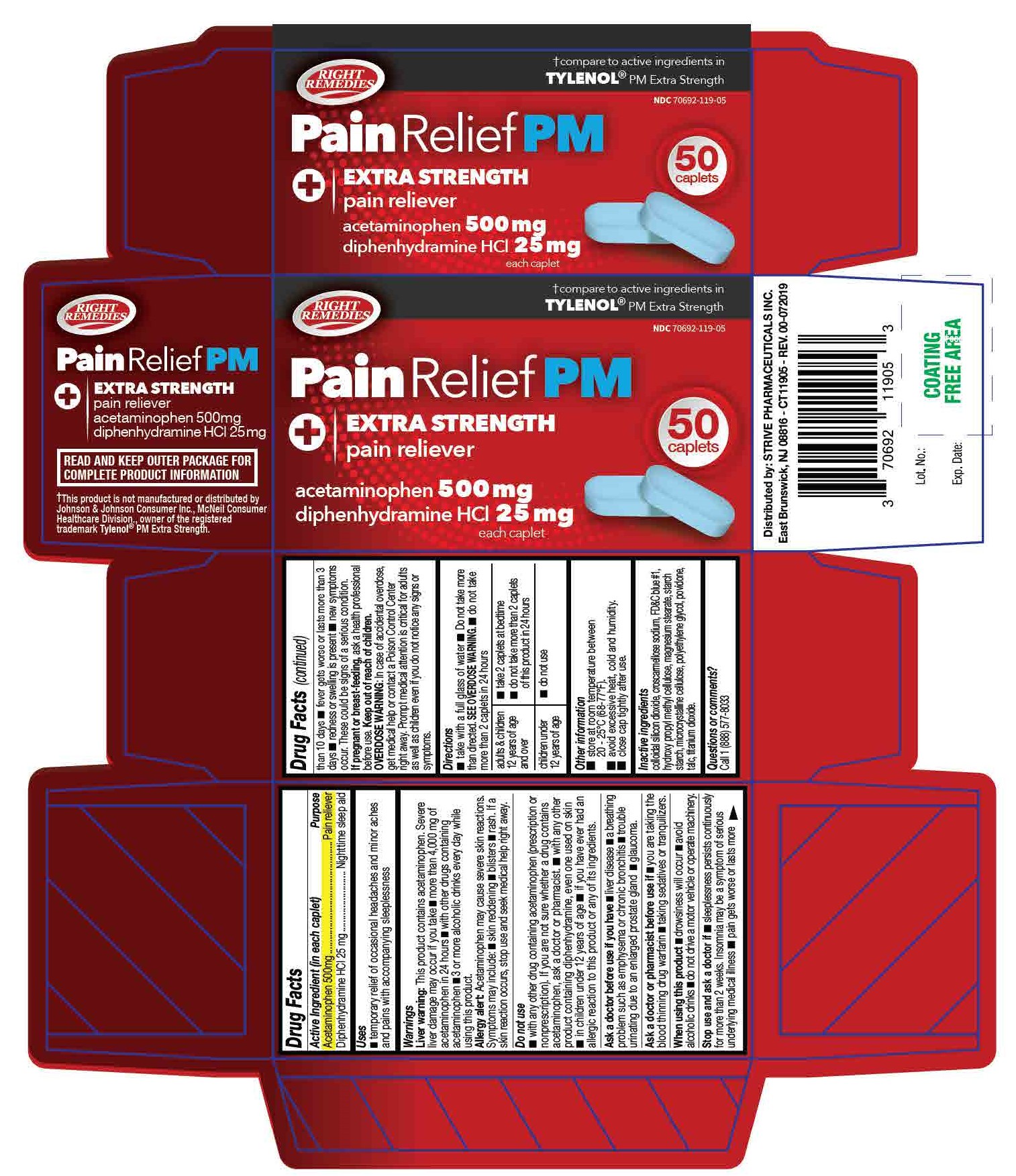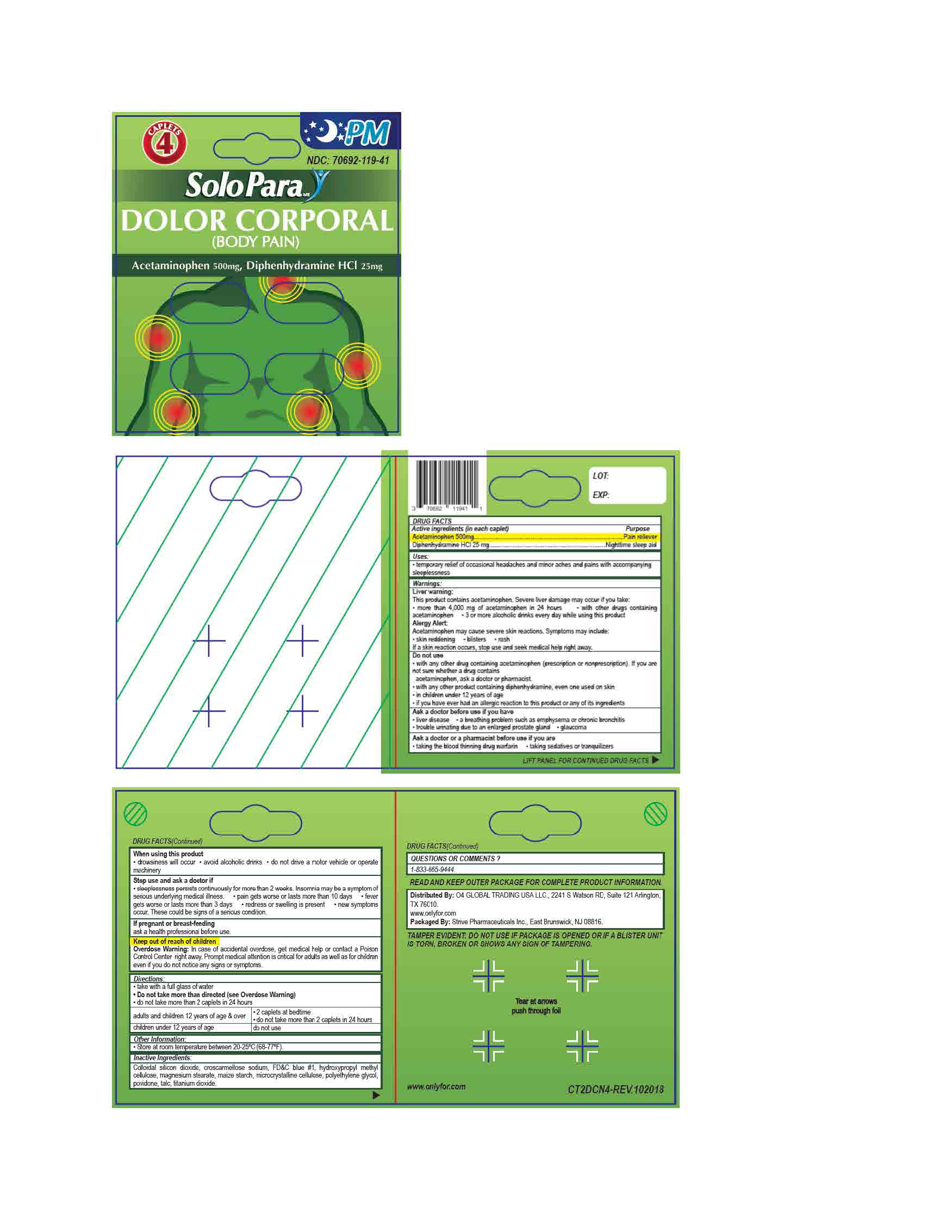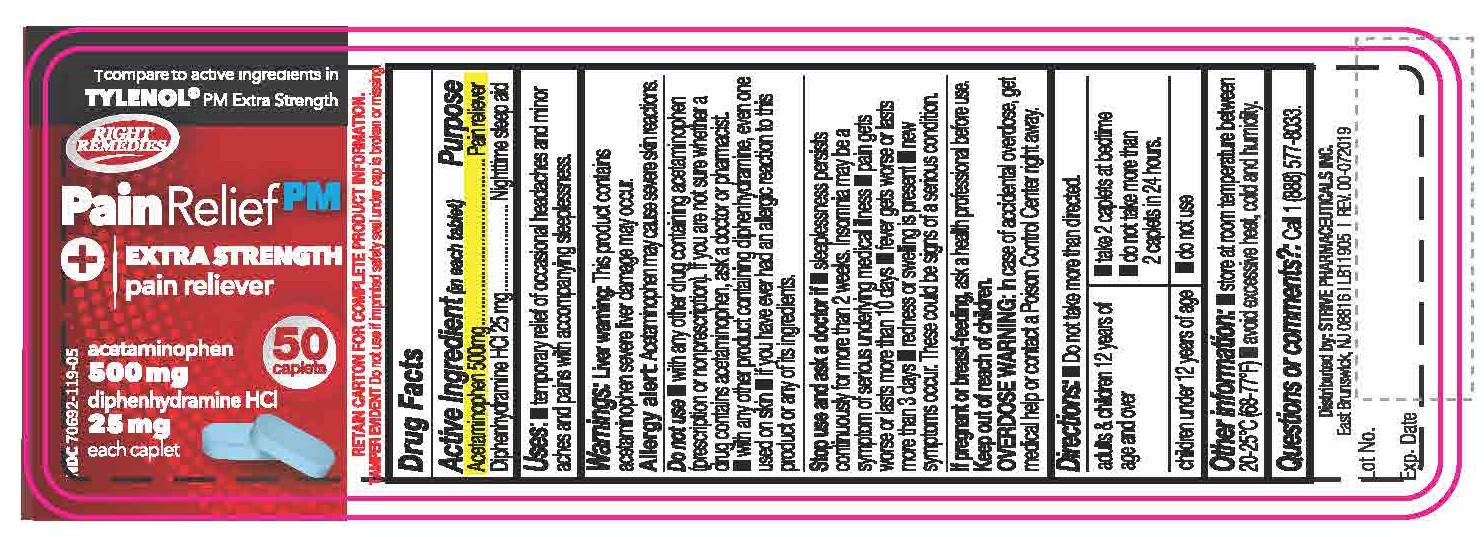 DRUG LABEL: Acetaminophen 500mg Diphenhydramine HCl 25mg
NDC: 70692-119 | Form: TABLET
Manufacturer: Strive Pharmaceuticals Inc
Category: otc | Type: HUMAN OTC DRUG LABEL
Date: 20201116

ACTIVE INGREDIENTS: DIPHENHYDRAMINE HYDROCHLORIDE 25 mg/1 1; ACETAMINOPHEN 500 mg/1 1
INACTIVE INGREDIENTS: CROSCARMELLOSE SODIUM; POLYETHYLENE GLYCOL 400; POVIDONE; FD&C BLUE NO. 1; MICROCRYSTALLINE CELLULOSE; SILICON DIOXIDE; HYPROMELLOSES; MAGNESIUM STEARATE; STARCH, CORN; TALC; TITANIUM DIOXIDE

Pain Relief PM - Extra Strength
Body Pain - Dolor Corporal
(Acetaminophen 500mg; Diphenhydramine Hydrochloride 25mg)

ACTIVE INGREDIENT

Acetaminophen 500mg; Diphenhydramine 25mg

INACTIVE INGREDIENT

colloidal silicon dioxide, croscarmellose sodium, FD&C blue #1, hydroxypropyl methyl cellulose, magnesium stearate, maize starch, microcrystalline cellulose, polyethylene glycol, povidone, talc, titanium dioxide

DOSAGE AND ADMINISTRATION

- take with a full glass of water
- do not take more than directed
- do not take more than 2 caplets in 24 hours

adults and children 12 years of age and over | - 2 caplets at bedtime - do not take more than 2 caplets in 24 hours
children under 12 years of age | do not use

INDICATIONS AND USAGE

*temporarily relief of occasional heaches and minor aches and pains with accompanying sleeplessness

WARNINGS

Liver warning:

This product contains acetaminophen. Severe liver damage may occur if you take:

- more than 4000mg of acetaminophen in 24 hours
- with other drugs containing acetaminophen
- 3 or more alcoholic drinks every day while using this product

Allergy alert:

Acetaminophen may cause severe skin reactions. Symptoms may include:

- skin reddening
- blisters
- rash

if a skin reaction occurs, stop use and seek medical help right away

Do not use

- with any other drug containing acetaminophen (prescription or non prescription). If you are not sure whether a drug contains acetaminophen, ask a doctor or pharmacist
- with any other product containing diphenhydramine, even one used on skin
- in children under 12 years of age
- if youhave ever had an allergic reaction to this product or any of its ingredients

Ask a doctor before use if you have

- liver disease
- a breathing problem such as emphysema or chronic bronchitis
- trouble urinating due to an enlarged prostrate gland
- glaucoma

Ask a doctor or a pharmacist before use if you are

- taking the blood thinning drug warfarin
- taking sedatives or tranquilizers

When using this product

- drowsiness will occur
- avoi alcoholic drinks
- do not drive a motor vehicle or operate machinery

Stop use and ask a doctor if

- sleeplessness persists continuously for more than 2 weeks. Insomnia may be a symptom of serious underlying medical illness
- pain gets worse or lasts more than 10 days
- fever gets worse or lasts more than 3 days
- new symptoms occur
- redness or swelling is present

These could be signs of a serious condition

If pregnant or breast-feeding,

ask a health professional before use

Keep out of reach of children

Overdose warning: In case of accidental overdose, get medical help or contact a Poison Control Center right away. Prompt medical attention is critical for adults as well as for children even if you do not notice any signs or symptoms.

Keep out of reach of children

Overdose Warning: In case of accidental overdose, get medical help or contact a Poison Control Center right away. Prompt medical attention is critical for adults as well as for children even if you do not notice any signs or symptoms.

PURPOSE

Pain reliever

Nighttime sleep-aid

OTHER SAFETY INFORMATION

- store at room temperature between 20ºC - 25ºC (68ºF - 77ºF)